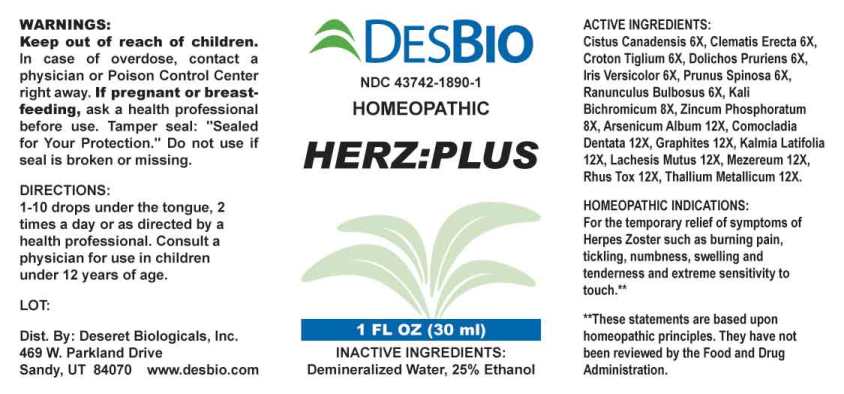 DRUG LABEL: Herz Plus
NDC: 43742-1890 | Form: LIQUID
Manufacturer: Deseret Biologicals, Inc.
Category: homeopathic | Type: HUMAN OTC DRUG LABEL
Date: 20240911

ACTIVE INGREDIENTS: HELIANTHEMUM CANADENSE 6 [hp_X]/1 mL; CLEMATIS RECTA FLOWERING TOP 6 [hp_X]/1 mL; CROTON TIGLIUM SEED 6 [hp_X]/1 mL; MUCUNA PRURIENS FRUIT TRICHOME 6 [hp_X]/1 mL; IRIS VERSICOLOR ROOT 6 [hp_X]/1 mL; PRUNUS SPINOSA FLOWER BUD 6 [hp_X]/1 mL; RANUNCULUS BULBOSUS WHOLE 6 [hp_X]/1 mL; POTASSIUM DICHROMATE 8 [hp_X]/1 mL; ZINC PHOSPHIDE 8 [hp_X]/1 mL; ARSENIC TRIOXIDE 12 [hp_X]/1 mL; COMOCLADIA DENTATA BARK/LEAF 12 [hp_X]/1 mL; GRAPHITE 12 [hp_X]/1 mL; KALMIA LATIFOLIA LEAF 12 [hp_X]/1 mL; LACHESIS MUTA VENOM 12 [hp_X]/1 mL; DAPHNE MEZEREUM BARK 12 [hp_X]/1 mL; TOXICODENDRON PUBESCENS LEAF 12 [hp_X]/1 mL; THALLIUM 12 [hp_X]/1 mL
INACTIVE INGREDIENTS: WATER; ALCOHOL

DRUG FACTS:

ACTIVE INGREDIENTS:

Cistus Canadensis 6X, Clematis Erecta 6X, Croton Tiglium 6X, Dolichos Pruriens 6X, Iris Versicolor 6X, Prunus Spinosa 6X, Ranunculus Bulbosus 6X, Kali Bichromicum 8X, Zincum Phosphoratum 8X, Arsenicum Album 12X, Comocladia Dentata 12X, Graphites 12X, Kalmia Latifolia 12X, Lachesis Mutus 12X, Mezereum 12X, Rhus Tox 12X, Thallium Metallicum 12X.

HOMEOPATHIC INDICATIONS:

For the temporary relief of symptoms of Herpes Zoster such as burning pain, tickling, numbness, swelling and tenderness and extreme sensitivity to touch.**

**These statements are based upon homeopathic principles. They have not been reviewed by the Food and Drug Administration.

WARNINGS:

Keep out of reach of children. In case of overdose, contact a physician or Poison Control Center right away.

If pregnant or breast-feeding, ask a health professional before use.

Tamper seal: "Sealed for Your Protection." Do not use if seal is broken or missing.

Keep out of reach of children. In case of overdose, contact a physician or Poison Control Center right away.

DIRECTIONS:

1-10 drops under the tongue, 2 times a day or as directed by a health professional. Consult a physician for use in children under 12 years of age.

HOMEOPATHIC INDICATIONS:

For the temporary relief of symptoms of Herpes Zoster such as burning pain, tickling, numbness, swelling and tenderness and extreme sensitivity to touch.**

**These statements are based upon homeopathic principles. They have not been reviewed by the Food and Drug Administration.

INACTIVE INGREDIENTS:

Demineralized Water, 25% Ethanol

QUESTIONS:

Dist. By: Deseret Biologicals, Inc.

469 W. Parkland Drive

Sandy, UT 84070 www.desbio.com

PACKAGE LABEL DISPLAY:

DESBIO

NDC 43742-1890-1

HOMEOPATHIC

HERZ:PLUS

1 FL OZ (30 ml)